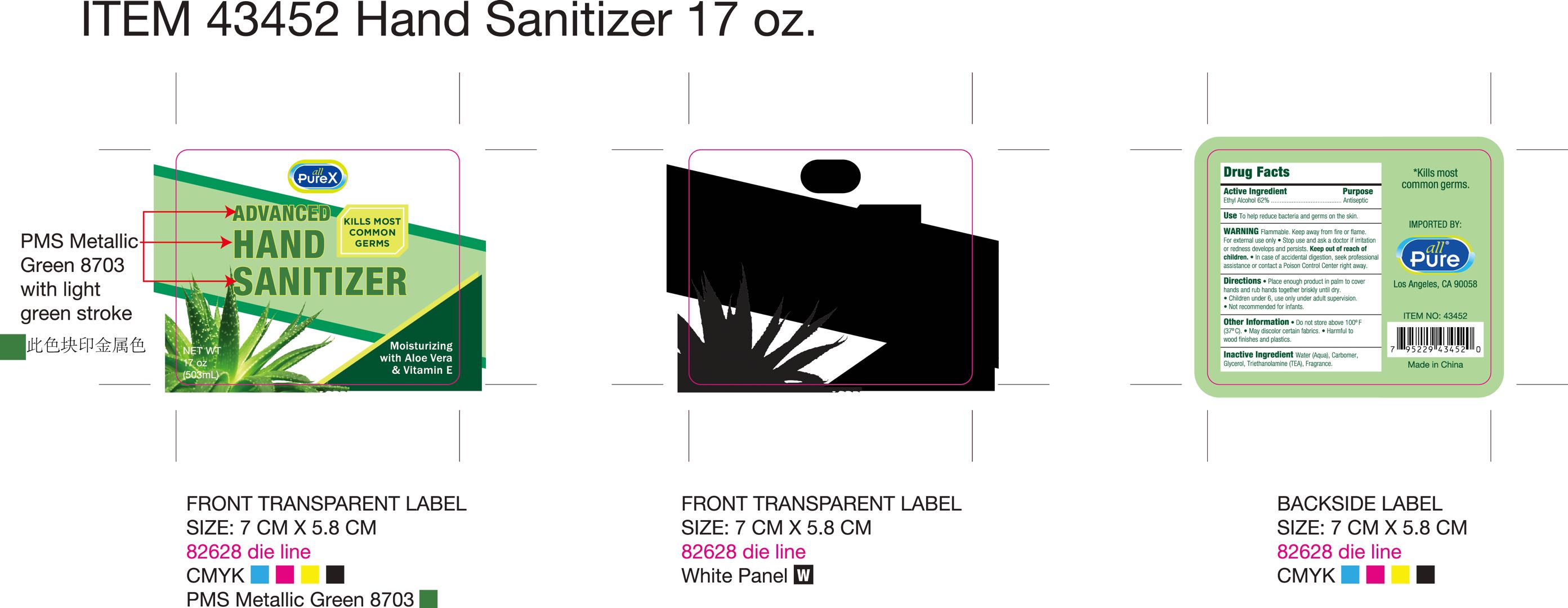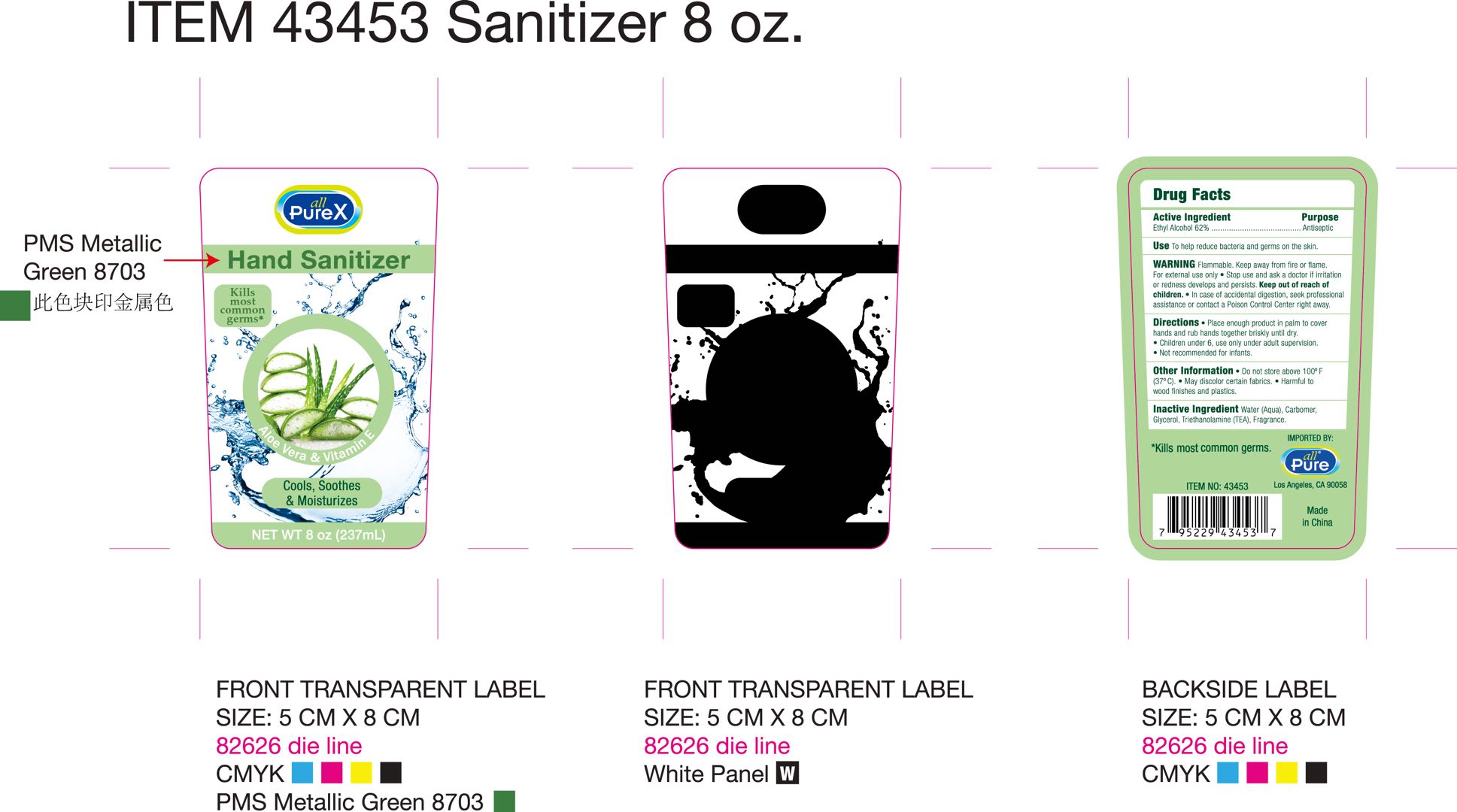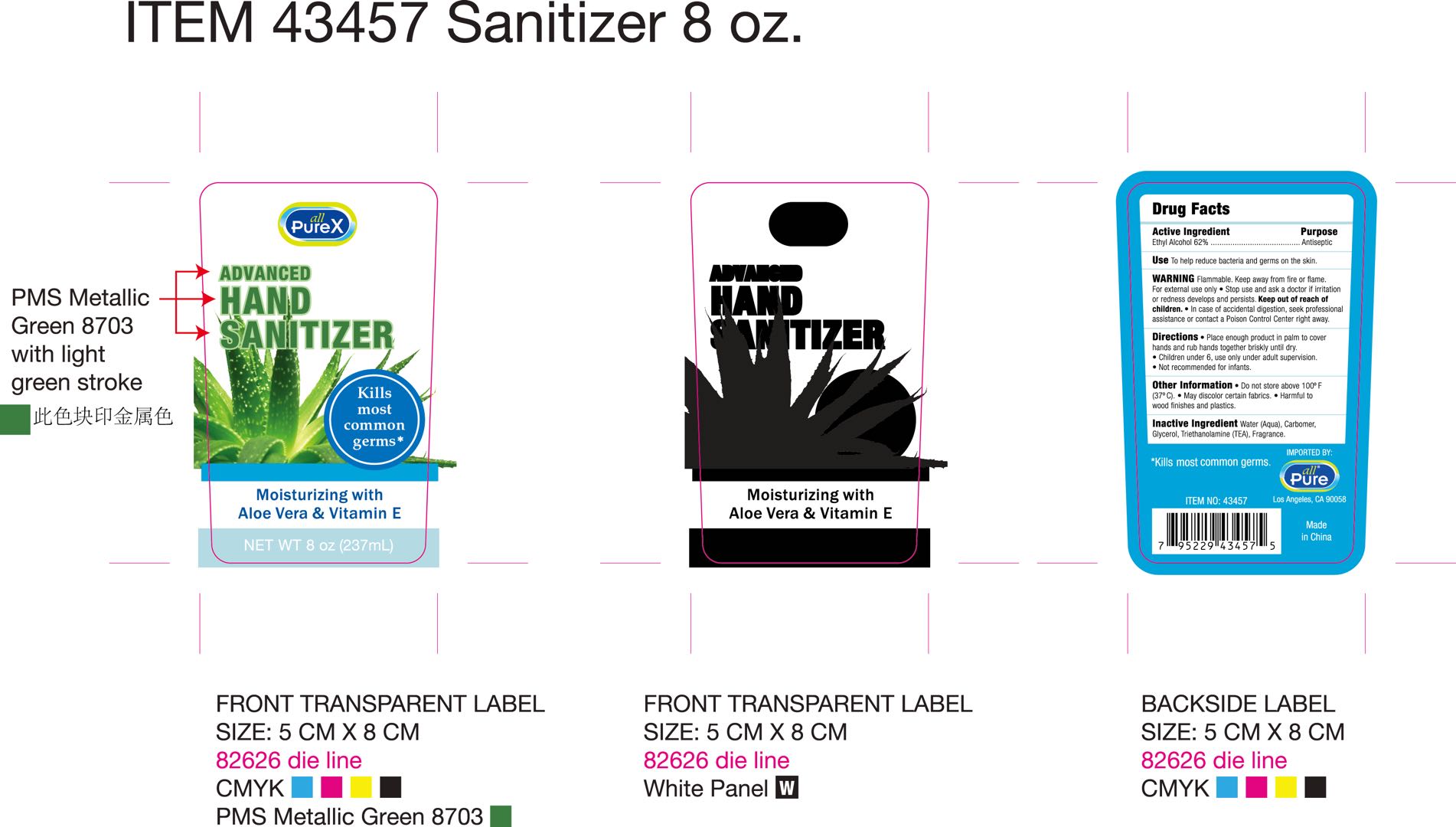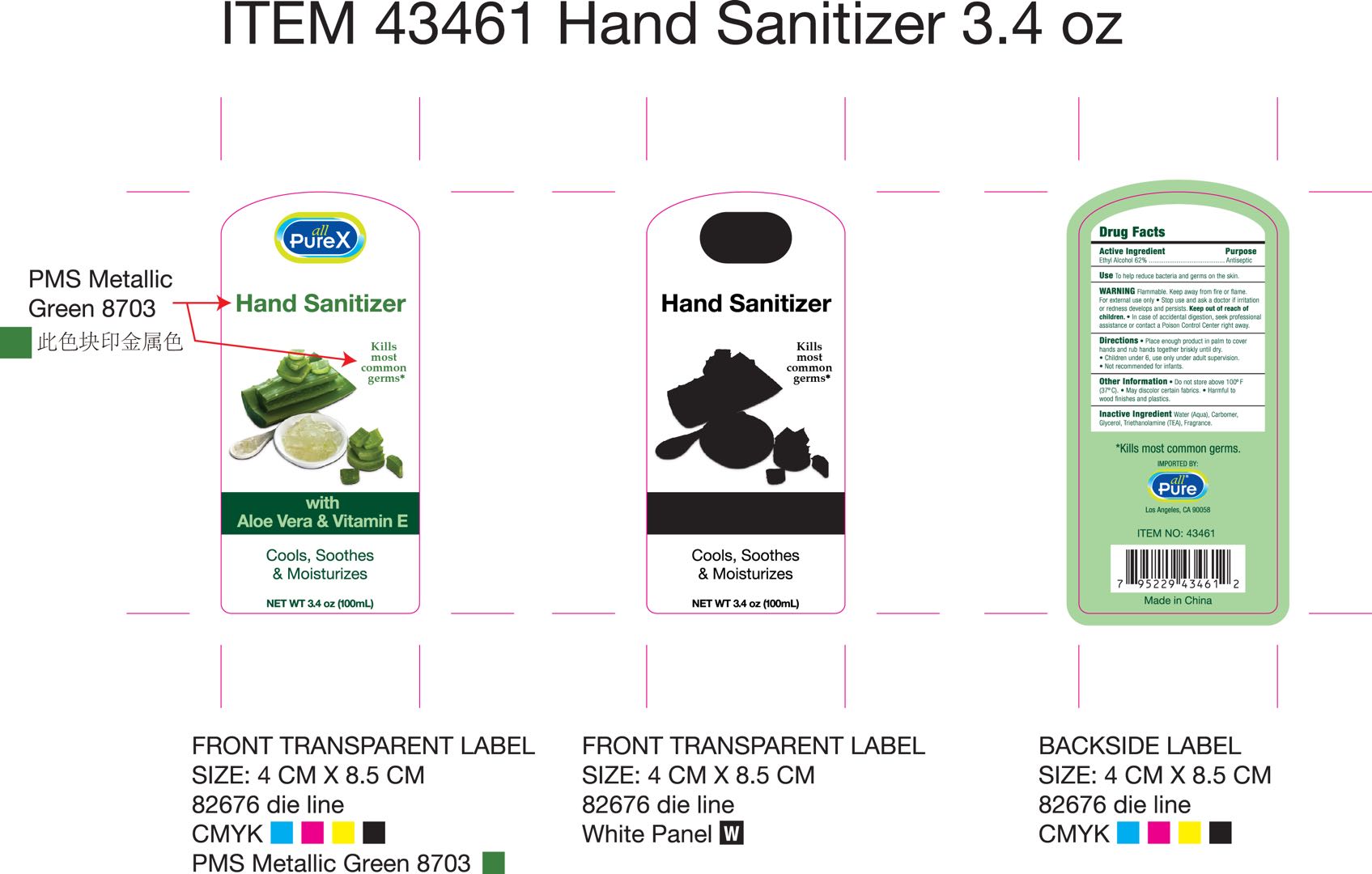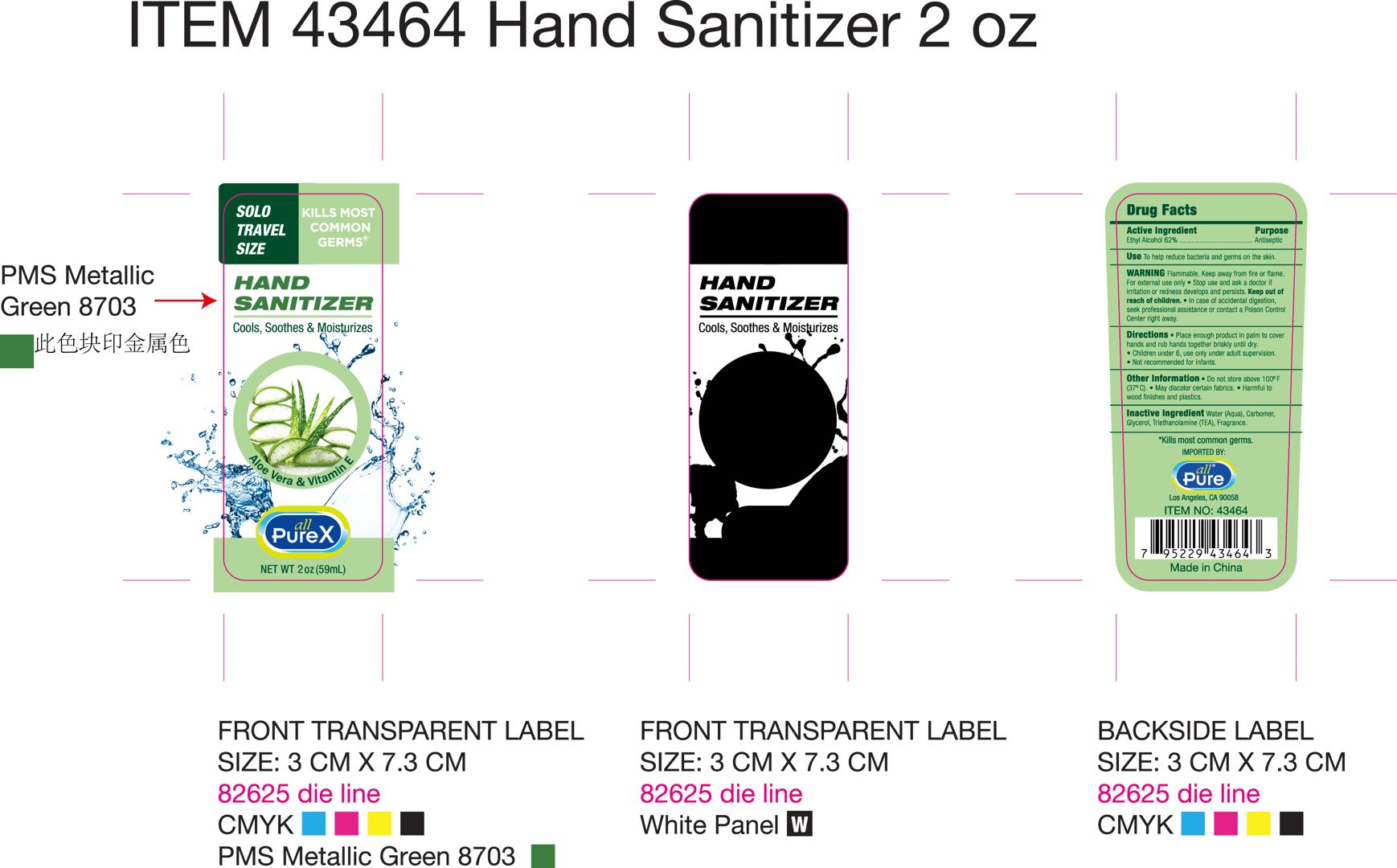 DRUG LABEL: HAND SANITIZER
NDC: 76681-012 | Form: GEL
Manufacturer: Taizhou Huangyan Delishi Daily Necessity Co., Ltd.
Category: otc | Type: HUMAN OTC DRUG LABEL
Date: 20200610

ACTIVE INGREDIENTS: ALCOHOL 75 mL/100 mL
INACTIVE INGREDIENTS: FRAGRANCE LAVENDER & CHIA F-153480; WATER; GLYCERIN; TRIETHANOLAMINE DODECYLBENZENESULFONATE; CARBOMER 934

HAND SANITIZER

Active Ingredient(s)

Ethyl Alcohol 62% v/v

Purpose

Antiseptic

Use

To help reduce bacteria and germs on the skin

Do not use

In children less than 2 month of age. On open skin wounds

WHEN USING

/

STOP USE

If irritation or rash occurs. These may be signs of a serious condition.

KEEP OUT OF REACH OF CHILDREN

If swallowed, get medical hep or contact a Poison Control Center right away.

Directions

Place enough product in palm to cover hands and Rub hands together briskly until dry.

Children under 6,use only under adult suoervision.

Not recommended for infants.

Inactive ingredients

Water (Aqua), Carbomer, Glycerol, Triethanolamine(TEA), Fragrance